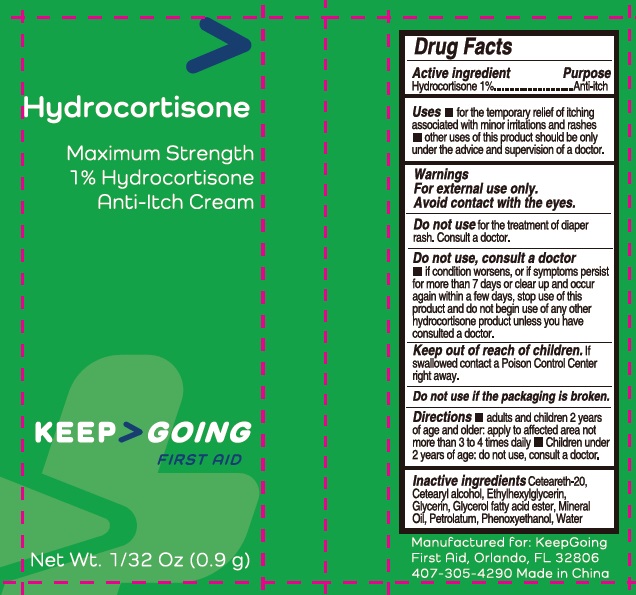 DRUG LABEL: Hydrocortisone
NDC: 43473-049 | Form: CREAM
Manufacturer: Nantong Health & Beyond Hygienic Products Inc.
Category: otc | Type: HUMAN OTC DRUG LABEL
Date: 20240808

ACTIVE INGREDIENTS: HYDROCORTISONE 10 mg/1 g
INACTIVE INGREDIENTS: CETOSTEARYL ALCOHOL; POLYOXYL 20 CETOSTEARYL ETHER; ETHYLHEXYLGLYCERIN; GLYCERIN; MINERAL OIL; PETROLATUM; PHENOXYETHANOL; WATER

43473-049-01_Hydrocortisone

Active ingredient

Hydrocortisone 1%

Purpose

Anti-itch

Uses

- for the temporary relief of itching associated with minor irritations and rashes
- other uses of this product should be only under the advice and superivision of a doctor.

Warnings

For external use only.

Avoid contact with the eyes.

Do not use

for the treatment of diaper rash. Consult a doctor.

Do not use, consult a doctor

if condition worsens, or if symptoms persist for more than 7 days or clear up and occur again within a few days, stop use of this product and do not begin use of any other hydrocortisone product unless you have consulted a doctor.

Do not use if the packaging is broken

Keep out of reach of children.

If swallowed contact a Poison Control Center right away.

Directions

- adults and children 2 years of age and older: apply to affected area not more than 3 to 4 times daily
- children under 2 years of age: do not use.

Inactive ingredients

Cetearyl alcohol, Ceteareth-20, Ethylhexylglycerin, Glycerin, Glycerol fatty acid ester, Mineral Oil, Petrolatum, Phenoxyethanol, Water